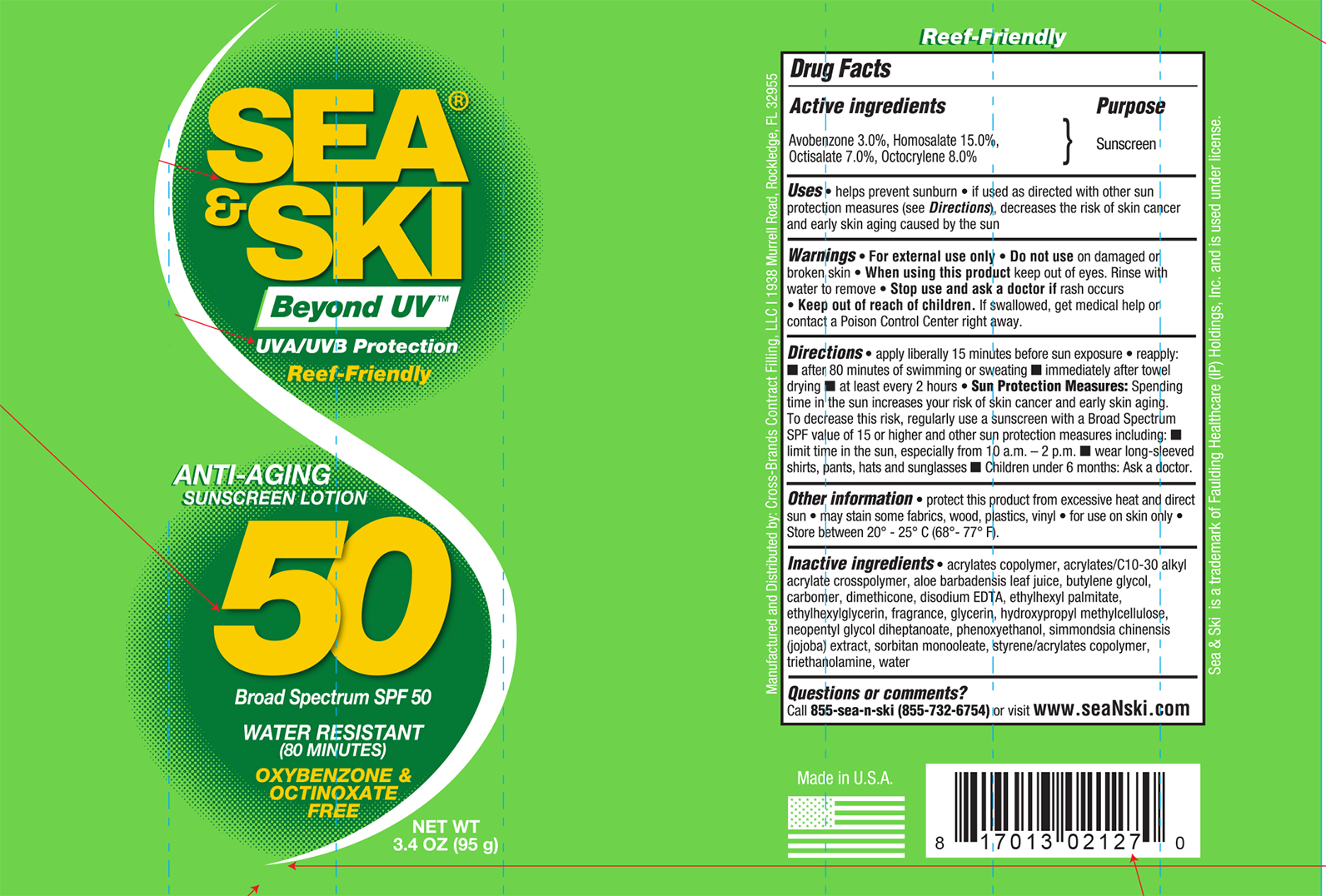 DRUG LABEL: Sea and Ski SPF 50
NDC: 73440-2127 | Form: LOTION
Manufacturer: Cross-Brands Contract Filling
Category: otc | Type: HUMAN OTC DRUG LABEL
Date: 20210219

ACTIVE INGREDIENTS: HOMOSALATE 14.25 g/95 g; OCTOCRYLENE 7.6 g/95 g; AVOBENZONE 2.85 g/95 g; OCTISALATE 6.65 g/95 g
INACTIVE INGREDIENTS: WATER 46.83 g/95 g

Sea&Ski SPF 50 3.4oz